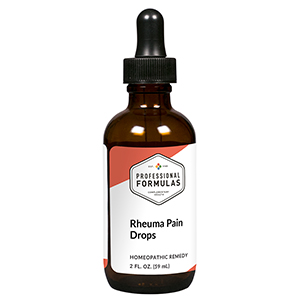 DRUG LABEL: Rheuma Pain Drops
NDC: 63083-2057 | Form: LIQUID
Manufacturer: Professional Complementary Health Formulas
Category: homeopathic | Type: HUMAN OTC DRUG LABEL
Date: 20190815

ACTIVE INGREDIENTS: BRYONIA ALBA ROOT 3 [hp_X]/59 mL; COLCHICUM AUTUMNALE BULB 3 [hp_X]/59 mL; SOLANUM DULCAMARA WHOLE 4 [hp_X]/59 mL; RHODODENDRON TOMENTOSUM LEAFY TWIG 4 [hp_X]/59 mL; RANUNCULUS BULBOSUS WHOLE 4 [hp_X]/59 mL; APIS MELLIFERA 6 [hp_X]/59 mL; AMARYLLIS BELLADONNA WHOLE 6 [hp_X]/59 mL; CAUSTICUM 6 [hp_X]/59 mL; FORMICA RUFA 6 [hp_X]/59 mL; KALMIA LATIFOLIA LEAF 6 [hp_X]/59 mL; PHYTOLACCA AMERICANA ROOT 6 [hp_X]/59 mL; PULSATILLA MONTANA WHOLE 6 [hp_X]/59 mL; TOXICODENDRON PUBESCENS LEAF 6 [hp_X]/59 mL
INACTIVE INGREDIENTS: ALCOHOL; WATER

C57

ACTIVE INGREDIENTS

Bryonia 3X
Colchicum autumnale 3X
Dulcamara 4X
Ledum palustre 4X
Ranunculus bulbosus 4X
Apis mellifica 6X
Belladonna 6X
Causticum 6X
Formica rufa 6X
Kalmia latifolia 6X
Phytolacca decandra 6X
Pulsatilla 6X
Rhus toxicodendron 6X

QUESTIONS

Professional Formulas

PO Box 2034 Lake Oswego, OR 97035

INDICATIONS

For the temporary relief of mild pain or stiffness in joints, muscles, or surrounding tissue, particularly when improved by applying heat.*

PURPOSE

*Claims based on traditional homeopathic practice, not accepted medical evidence. Not FDA evaluated.

WARNINGS

In case of overdose, get medical help or contact a poison control center right away.

Keep out of the reach of children.

PREGNANCY OR BREAST FEEDING

If pregnant or breastfeeding, ask a healthcare professional before use.

DIRECTIONS

Place drops under tongue 30 minutes before/after meals. Adults and children 12 years and over: Take 10 drops up to 3 times per day for up to 6 weeks. For immediate onset of symptoms, take 10 to 15 drops every 15 minutes up to 3 hours. For less severe symptoms, take 10-15 drops hourly up to 8 hours. Consult a physician for use in children under 12 years of age.

OTHER INFORMATION

Tamper resistant. If seal is broken, do not use. After opening, close container tightly and store at room temperature away from heat.

INACTIVE INGREDIENTS

20% ethanol, purified water.

LABEL

Est 1985

Professional Formulas

Complementary Health

Rheuma Pain Drops

Homeopathic Remedy

2 FL. OZ. (59 mL)